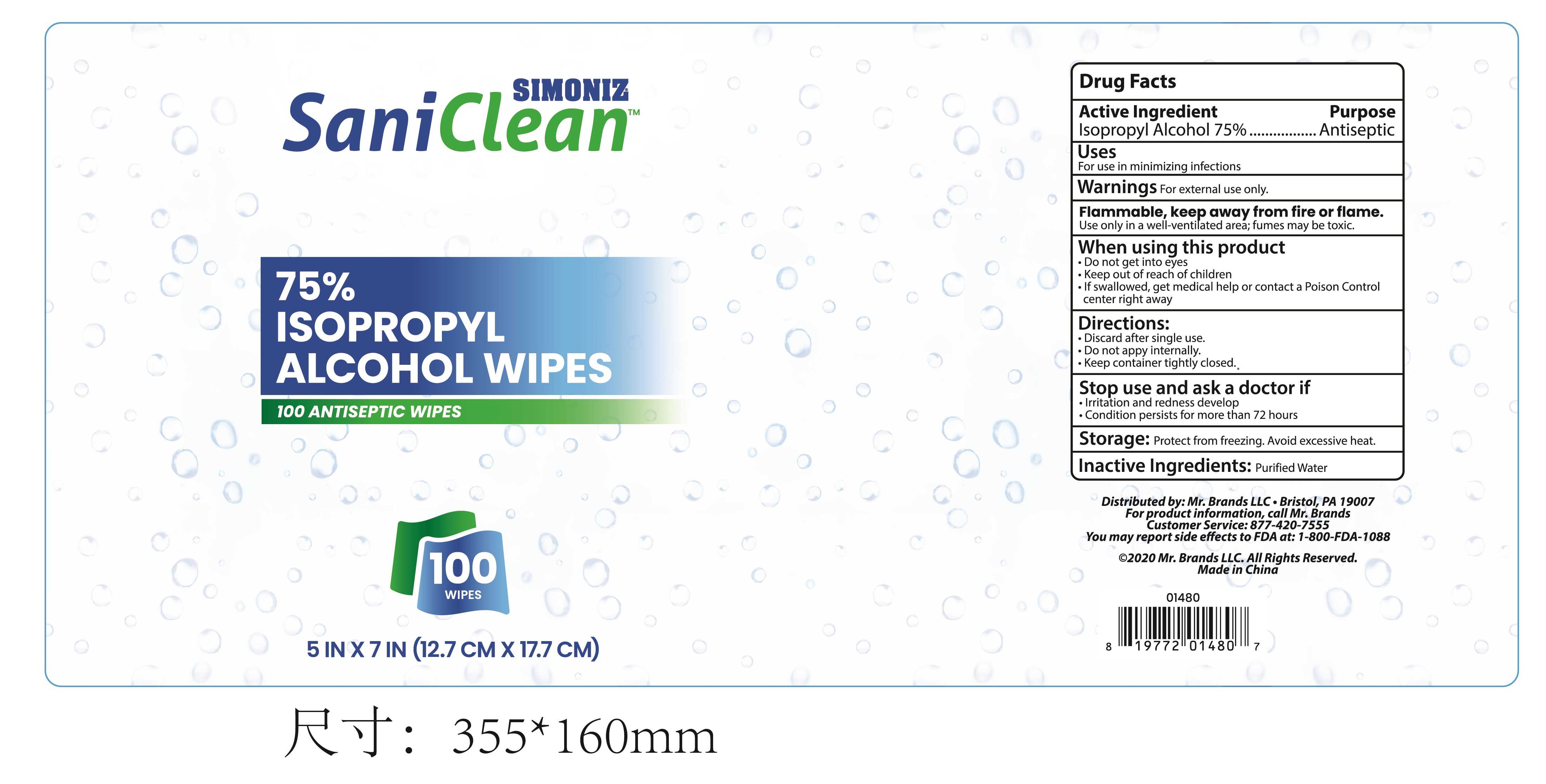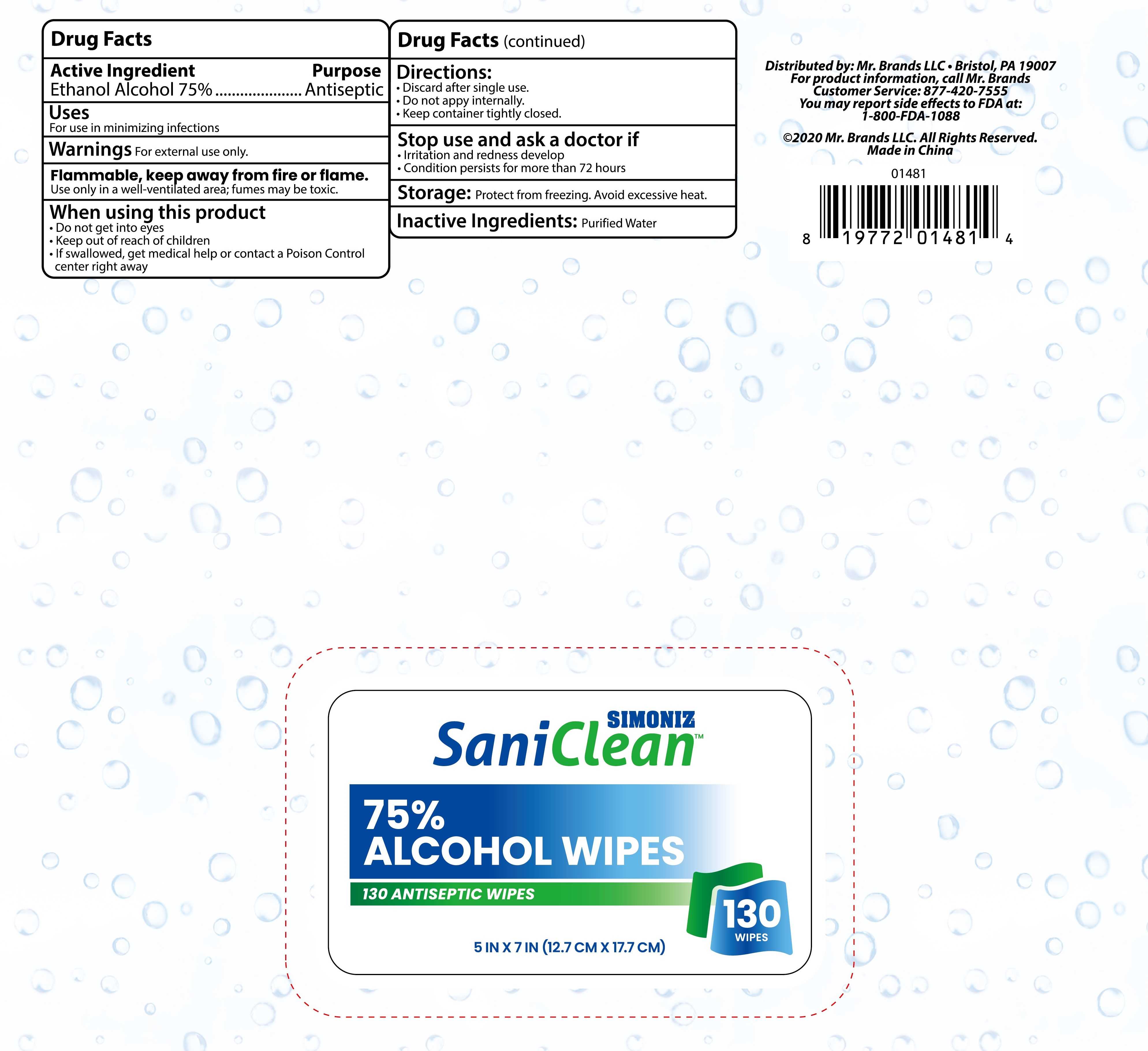 DRUG LABEL: Sani Clean
NDC: 76991-013 | Form: CLOTH
Manufacturer: Hefei Wenqi Industrial & Trade Co., Ltd
Category: otc | Type: HUMAN OTC DRUG LABEL
Date: 20200923

ACTIVE INGREDIENTS: ALCOHOL 75 mL/100 1
INACTIVE INGREDIENTS: WATER

76991-013
Sani Clean

Active Ingredient(s)

Ethanol Alcohol 75%

Purpose

Antiseptic

Use

For use in minimizing infections

Warnings

For external use only.
Flammable, keep away from fire or flame.
Use only in a well-ventifated area; fumes may be toxic.

When using this product
Do not get into eyes

Keep out of reach of children
If swallowed, get medical help or contact a Poison Control center right away

Do not use

Do not get into eyes

Do not appy internally.

When using this product
Do not get into eyes

Keep out of reach of children
If swallowed, get medical help or contact a Poison Control center right away

Stop use and ask a doctor if
Irritation and redness develop
Condition persists for more than 72 hours
Storage: Protect from freezing. Avoid excessive heat.

Keep out of reach of children
If swallowed, get medical help or contact a Poison Control center right away

Directions

Discard after single use.
Do not appy internally.
Keep container tightly closed.

Other information

/

Inactive ingredients

Purified Water